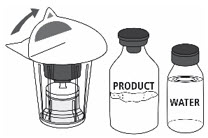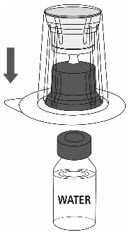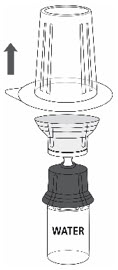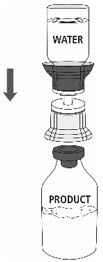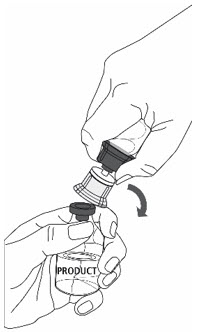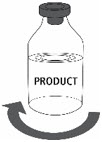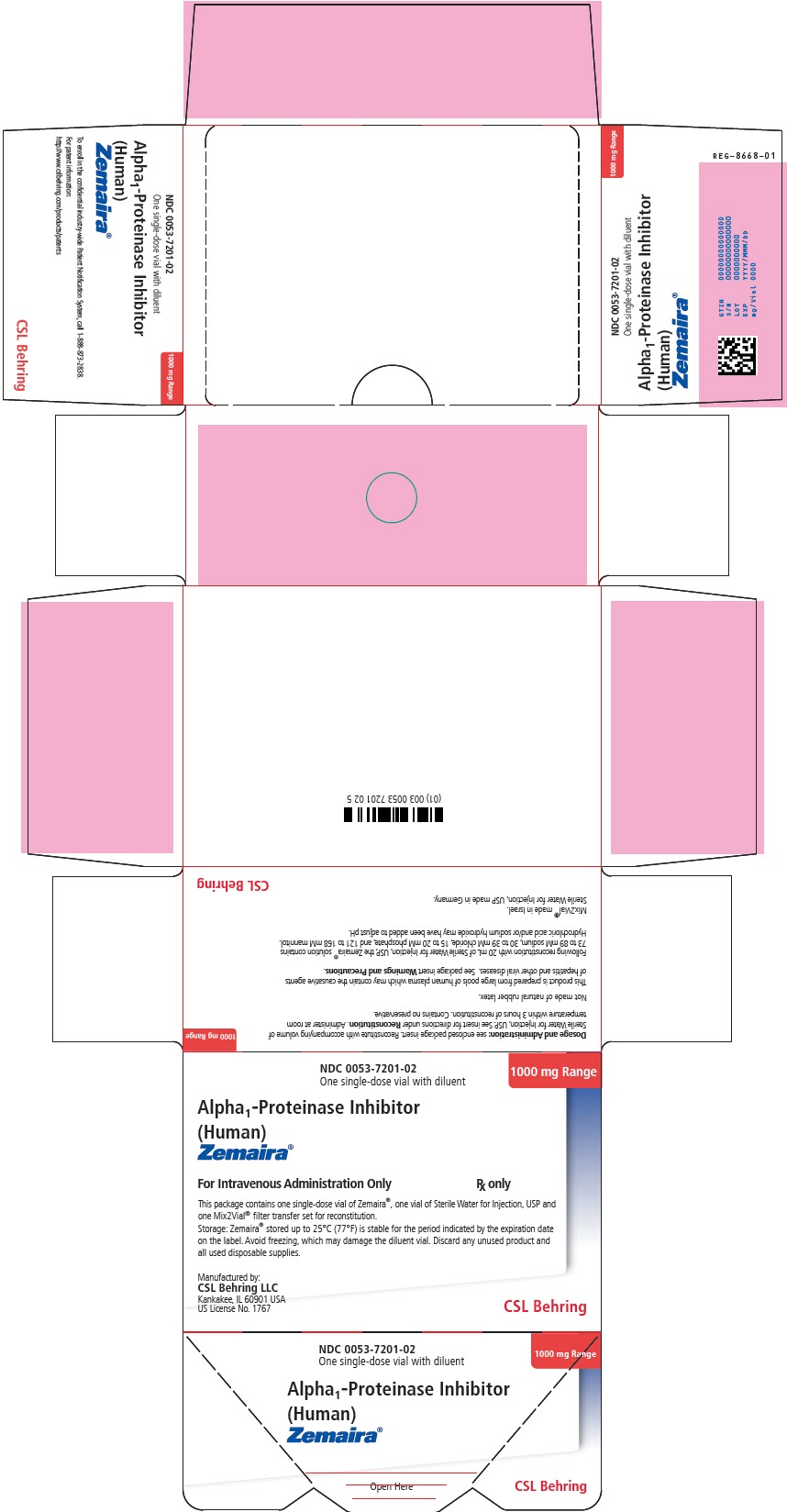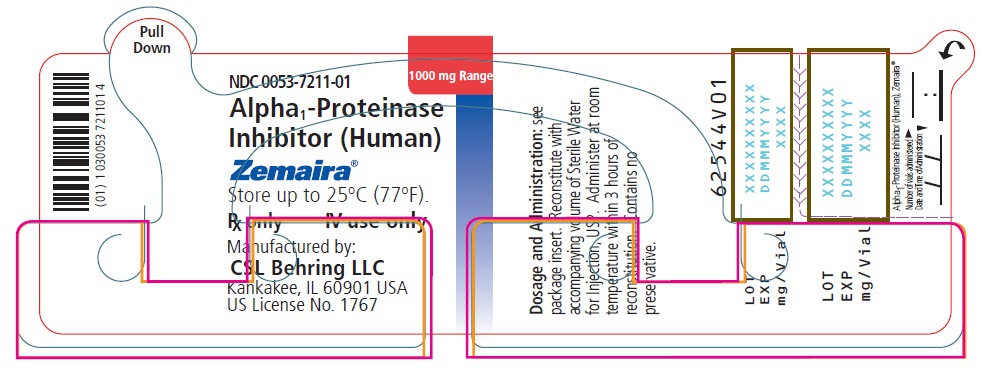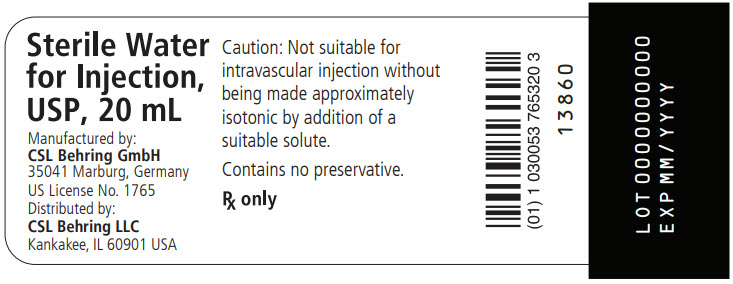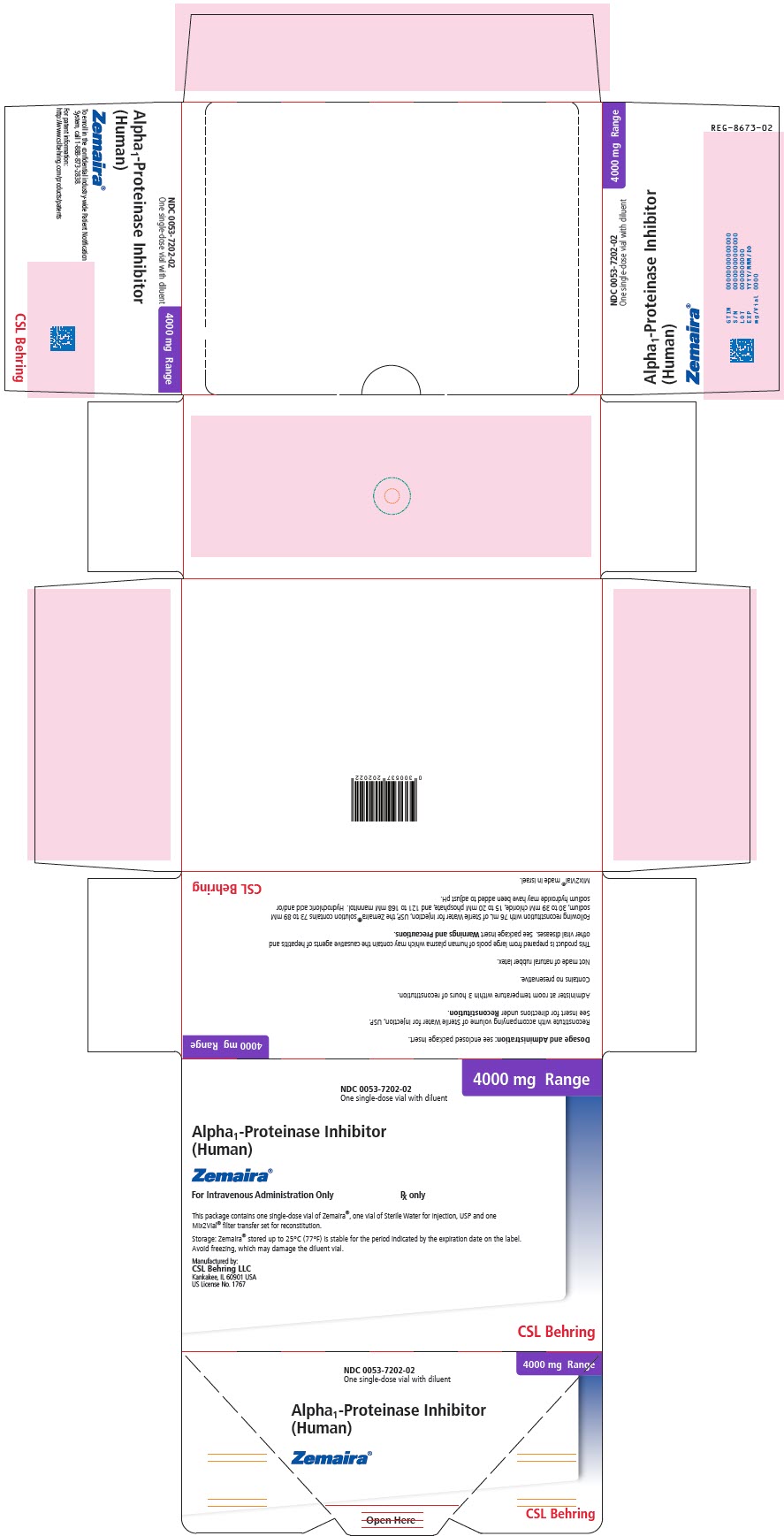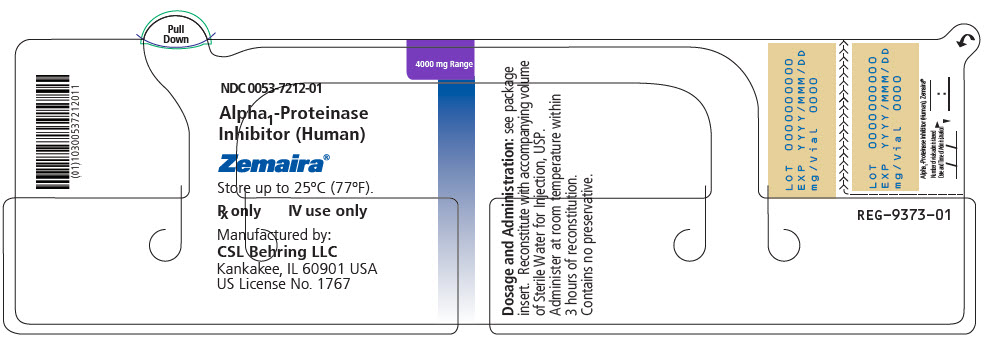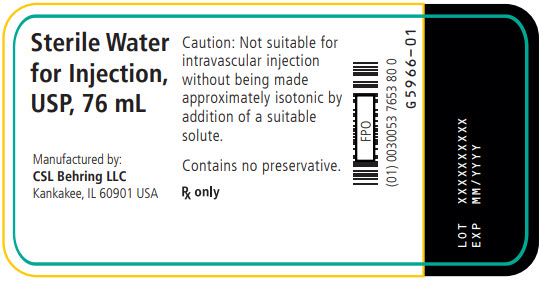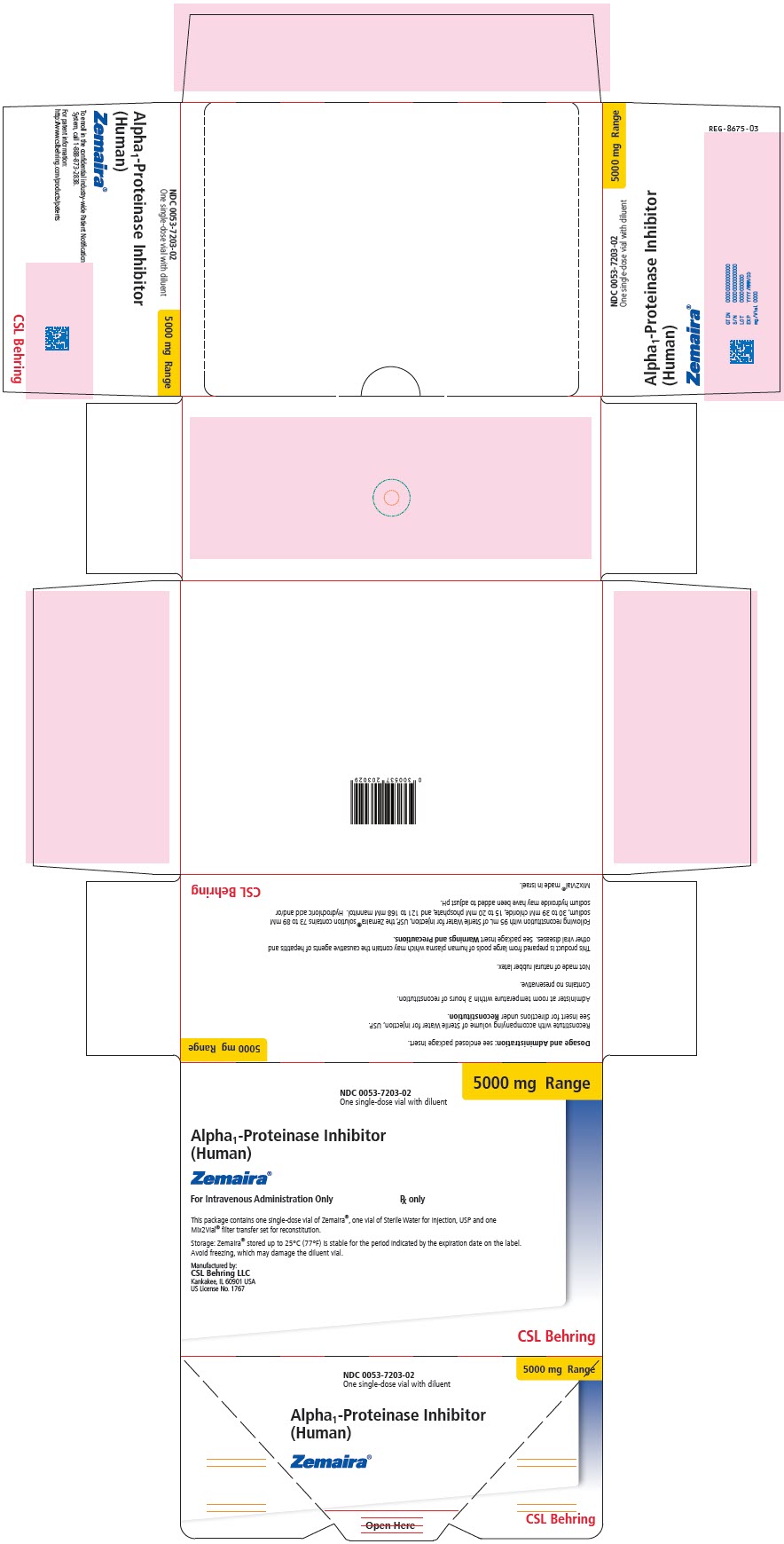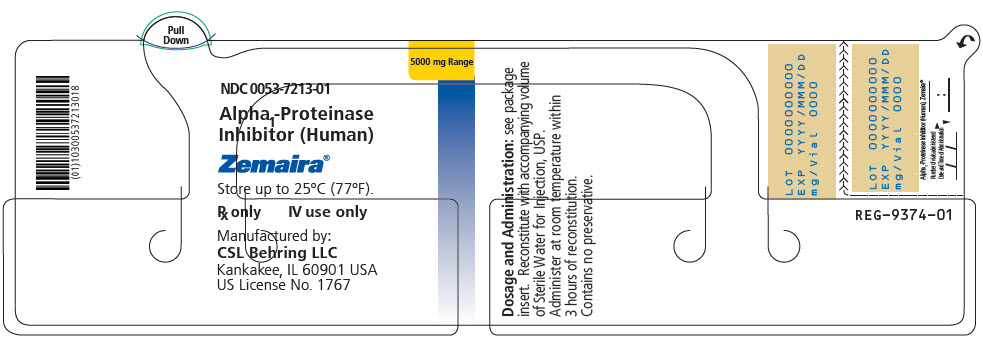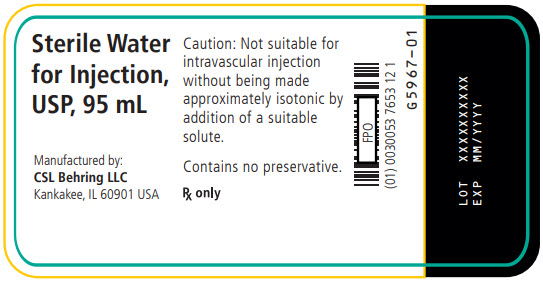 DRUG LABEL: Zemaira
NDC: 0053-7201 | Form: KIT | Route: INTRAVENOUS
Manufacturer: CSL Behring LLC
Category: other | Type: PLASMA DERIVATIVE
Date: 20240923

ACTIVE INGREDIENTS: .ALPHA.1-PROTEINASE INHIBITOR HUMAN 1000 mg/20 mL
INACTIVE INGREDIENTS: Sodium Chloride 41 mg/20 mL; Sodium Phosphate 47 mg/20 mL; Mannitol 525 mg/20 mL; hydrochloric acid; sodium hydroxide; Water

HIGHLIGHTS OF PRESCRIBING INFORMATION

These highlights do not include all the information needed to use ZEMAIRA safely and effectively. See full prescribing information for ZEMAIRA.
ZEMAIRA® (alpha1-proteinase inhibitor (human))
lyophilized powder for reconstitution for intravenous use
Initial U.S. Approval: 2003

1 INDICATIONS AND USAGE

- ZEMAIRA is an alpha1-proteinase inhibitor (A1-PI) indicated for chronic augmentation and maintenance therapy in adults with A1-PI deficiency and clinical evidence of emphysema (1).
- The effect of augmentation therapy with ZEMAIRA or any A1-PI product on pulmonary exacerbations and on the progression of emphysema in A1-PI deficiency has not been demonstrated in randomized, controlled clinical studies (1).
- ZEMAIRA is not indicated as therapy for lung disease patients in whom severe A1-PI deficiency has not been established (1).

2 DOSAGE AND ADMINISTRATION

For intravenous use after reconstitution only (2).

- The recommended weekly dose of ZEMAIRA is 60 mg/kg body weight. Dose ranging studies using efficacy endpoints have not been performed with ZEMAIRA or any A1-PI product (2).
- Administer through a suitable 5 micron infusion filter (not supplied) at room temperature within 3 hours after reconstitution (2.2).
- Do not mix with other medicinal products. Administer through a separate dedicated infusion line (2.2).
- Administer at a rate of approximately 0.08 mL/kg/min as determined by the response and comfort of the patient (2.2).
- Monitor closely the infusion rate and the patient's clinical state, including vital signs, throughout the infusion. Slow or stop the infusion if adverse reactions occur. If symptoms subside promptly, the infusion may be resumed at a lower rate that is comfortable for the patient (2.2).

3 DOSAGE FORMS AND STRENGTHS

ZEMAIRA is supplied in a single-dose vial containing approximately 1000 mg, 4000 mg, or 5000 mg of functionally active A1-PI as a white to off-white lyophilized powder for reconstitution with 20 mL, 76 mL, or 95 mL of Sterile Water for Injection, USP. The amount of functional A1-PI is printed on the vial label and carton (3).

4 CONTRAINDICATIONS

- History of anaphylaxis or severe systemic reactions to ZEMAIRA or A1-PI protein (4).
- Immunoglobulin A (IgA)-deficient patients with antibodies against IgA, due to the risk of severe hypersensitivity (4).

5 WARNINGS AND PRECAUTIONS

- Observe any signs of hypersensitivity such as tachycardia, hypotension, confusion, syncope, oxygen consumption decrease, and pharyngeal edema when administering ZEMAIRA to patients with known hypersensitivity to an A1-PI product (5.1).
- Patients with selective or severe IgA deficiency can develop antibodies to IgA and, therefore, have a greater risk of developing potentially severe hypersensitivity and anaphylactic reactions. If anaphylactic or severe anaphylactoid reactions occur, discontinue the infusion immediately (5.2).
- Because ZEMAIRA is made from human blood, it may carry a risk of transmitting infectious agents, e.g., viruses, the variant Creutzfeldt-Jakob disease (vCJD) agent and, theoretically, the Creutzfeldt-Jakob disease (CJD) agent (5.3).

6 ADVERSE REACTIONS

- Serious adverse reactions reported following administration of ZEMAIRA in pre-licensure clinical trials included one event each in separate subjects of bronchitis and dyspnea, and one event each in a single subject of chest pain, cerebral ischemia and convulsion.
- The most common adverse reactions occurring in at least 5% of subjects receiving ZEMAIRA in all pre-licensure clinical trials were headache, sinusitis, upper respiratory infection, bronchitis, asthenia, cough increased, fever, injection site hemorrhage, rhinitis, sore throat, and vasodilation (6).

To report SUSPECTED ADVERSE REACTIONS, contact CSL Behring Pharmacovigilance at 1-866-915-6958 or FDA at 1-800-FDA-1088 or www.fda.gov/medwatch.

FULL PRESCRIBING INFORMATION

1 INDICATIONS AND USAGE

ZEMAIRA is an alpha1-proteinase inhibitor (A1-PI) indicated for chronic augmentation and maintenance therapy in adults with A1-PI deficiency and clinical evidence of emphysema.

ZEMAIRA increases antigenic and functional (anti-neutrophil elastase capacity [ANEC]) serum levels and lung epithelial lining fluid (ELF) levels of A1-PI.

Clinical data demonstrating the long-term effects of chronic augmentation therapy of individuals with ZEMAIRA are not available.

The effect of augmentation therapy with ZEMAIRA or any A1-PI product on pulmonary exacerbations and on the progression of emphysema in A1-PI deficiency has not been demonstrated in randomized, controlled clinical studies.

ZEMAIRA is not indicated as therapy for lung disease patients in whom severe A1-PI deficiency has not been established.

2 DOSAGE AND ADMINISTRATION

For intravenous use after reconstitution only.

The recommended dose of ZEMAIRA is 60 mg/kg body weight administered once weekly. Dose ranging studies using efficacy endpoints have not been performed with ZEMAIRA or any A1-PI product.

2.1 Preparation and Reconstitution

- Check the expiration date on the vial label and carton. Do not use ZEMAIRA after the expiration date.
- Reconstitute prior to use according to the instructions provided below.
- Reconstitute ZEMAIRA using aseptic technique to maintain product sterility.
- Total reconstitution time for a 1g vial should be obtained within 5 minutes.
- Total reconstitution time for a 4g or 5g vial should be obtained within 10 minutes.
- Inspect the reconstituted solution prior to administration. The solution should be clear, colorless to slightly yellow, and free from visible particles.
- Reconstituted ZEMAIRA may be stored at room temperature. Do not freeze the reconstituted solution.

Follow the steps provided below for the preparation and reconstitution of ZEMAIRA:

1. Ensure that the ZEMAIRA vial and Sterile Water for Injection vial are at room temperature.
2. Remove the plastic flip-top cap from the Sterile Water for Injection vial.
3. Wipe the rubber stopper of the Sterile Water for Injection vial with antiseptic solution and allow it to dry.
4. Open the Mix2Vial® filter transfer set by peeling off the lid (Fig. 1). Do not remove the transfer set from the blister package.
  Fig. 1
5. Place the Sterile Water for Injection vial on an even, clean surface and hold the vial tight. Take the transfer set together with the blister package and vertically pierce the Sterile Water for Injection vial with the blue tip of the transfer set (Fig. 2).
  Fig. 2
6. Carefully remove the blister package from the transfer set by holding at the rim, and pulling vertically upwards. Make sure that you only pull away the blister package and not the transfer set (Fig. 3).
  Fig. 3
7. Remove the plastic flip-top cap from the ZEMAIRA vial.
8. Wipe the rubber stopper of the ZEMAIRA vial with antiseptic solution and allow it to dry.
9. Place the ZEMAIRA vial on an even and firm surface. Invert the Sterile Water for Injection vial with the transfer set attached and vertically pierce the ZEMAIRA vial with the clear tip of the transfer set (Fig. 4). The Sterile Water for Injection will automatically flow into the ZEMAIRA vial.

Note: Ensure all water has transferred into the ZEMAIRA vial.

Fig. 4

10. Follow steps below to remove entire transfer set from ZEMAIRA vial:
  - With one hand tightly grasp the ZEMAIRA vial as shown in Fig. 5.
  - With the other hand tightly grasp Sterile Water for Injection vial and blue transfer set.
  - Bend the entire transfer set to the side until it disconnects from the ZEMAIRA vial (Fig. 5).
  - Discard the Sterile Water for Injection vial with the entire transfer set.
  Fig. 5
11. Gently swirl the ZEMAIRA vial until the powder is completely dissolved (Fig. 6). DO NOT SHAKE. Take care not to touch the rubber vial stopper.
  Fig. 6

If more than 1 vial of ZEMAIRA is needed to achieve the required dose, use aseptic technique to transfer the reconstituted solution from the vials into the administration container (e.g., empty intravenous bag or glass bottle).

2.2 Administration

For intravenous use only.

- Do not mix ZEMAIRA with other medicinal products; administer ZEMAIRA through a separate dedicated infusion line.
- Perform a visual inspection of the reconstituted solution. The solution should be clear, colorless to slightly yellow, and free from visible particles.
- Administer at room temperature within 3 hours after reconstitution.
- Filter the reconstituted solution during administration. To ensure proper filtration of ZEMAIRA, use an intravenous administration set with a suitable 5 micron infusion filter (not supplied).
- Administer ZEMAIRA intravenously at a rate of approximately 0.08 mL/kg/min as determined by the response and comfort of the patient. The recommended dosage of 60 mg/kg body weight will take approximately 15 minutes to infuse.
- Monitor closely the infusion rate and the patient's clinical state, including vital signs, throughout the infusion. Slow or stop the infusion if adverse reactions occur. If symptoms subside promptly, the infusion may be resumed at a lower rate that is comfortable for the patient.
- ZEMAIRA is for single dose only. Following administration, discard any unused solution and all administration equipment in an appropriate manner as per local requirements.

3 DOSAGE FORMS AND STRENGTHS

ZEMAIRA is supplied in a single-dose vial containing approximately 1000 mg, 4000 mg, or 5000 mg of functionally active A1-PI as a white to off-white lyophilized powder for reconstitution with 20 mL, 76 mL, or 95 mL of Sterile Water for Injection, USP. The amount of functional A1-PI is printed on the vial label and carton.

4 CONTRAINDICATIONS

- ZEMAIRA is contraindicated in patients with a history of anaphylaxis or severe systemic reactions to ZEMAIRA or A1-PI protein.
- ZEMAIRA is contraindicated in immunoglobulin A (IgA)-deficient patients with antibodies against IgA, due to the risk of severe hypersensitivity [see Warnings and Precautions (5.2)].

5 WARNINGS AND PRECAUTIONS

5.1 Hypersensitivity to Other A1-PI Products

Observe any signs of hypersensitivity such as tachycardia, hypotension, confusion, syncope, oxygen consumption decrease, and pharyngeal edema when administering ZEMAIRA to patients with known hypersensitivity to an A1-PI product. If anaphylactic or severe anaphylactoid reactions occur, discontinue the infusion immediately. Have epinephrine and other appropriate supportive therapy available for the treatment of any acute anaphylactic or anaphylactoid reaction.

5.2 Hypersensitivity to IgA

ZEMAIRA may contain trace amounts of IgA. Patients with selective or severe IgA deficiency can develop antibodies to IgA and, therefore, have a greater risk of developing potentially severe hypersensitivity and anaphylactic reactions. If anaphylactic or severe anaphylactoid reactions occur, discontinue the infusion immediately. Have epinephrine and other appropriate supportive therapy available for the treatment of any acute anaphylactic or anaphylactoid reaction. ZEMAIRA is contraindicated in IgA-deficient patients with antibodies against IgA, due to the risk of severe hypersensitivity.

5.3 Transmissible Infectious Agents

Because ZEMAIRA is made from human blood, it may carry a risk of transmitting infectious agents, e.g., viruses, the variant Creutzfeldt-Jakob disease (vCJD) agent and, theoretically, the Creutzfeldt-Jakob disease (CJD) agent. The risk of infectious agent transmission has been reduced by screening plasma donors for prior exposure to certain viruses, testing for the presence of certain current virus infections, and including virus inactivation/removal steps in the manufacturing process for ZEMAIRA [see Description (11)]. Despite these measures, ZEMAIRA, like other products made from human blood, may still potentially contain human pathogenic agents, including those not yet known or identified. Thus, the risk of transmission of infectious agents cannot be totally eliminated.

All infections thought by a physician to have been possibly transmitted by this product should be reported by the physician or other healthcare provider to the CSL Behring Pharmacovigilance Department at 1-866-915-6958 or FDA at 1-800-FDA-1088 or www.fda.gov/medwatch.

6 ADVERSE REACTIONS

Serious adverse reactions reported following administration of ZEMAIRA in pre-licensure clinical trials included one event each in separate subjects of bronchitis and dyspnea, and one event each in a single subject of chest pain, cerebral ischemia and convulsion.

The most common adverse reactions (ARs) occurring in at least 5% of subjects receiving ZEMAIRA in all pre-licensure clinical trials were headache, sinusitis, upper respiratory infection, bronchitis, asthenia, cough increased, fever, injection site hemorrhage, rhinitis, sore throat, and vasodilation.

Serious adverse reactions identified during postmarketing use were hypersensitivity reactions [see Warnings and Precautions (5.1)].

In post-licensure trials, the exposure adjusted incidence rate (EAIR) of serious exacerbations of chronic obstructive pulmonary disease (COPD) among subjects was higher during the RAPID Extension trial as compared to the rate observed during the preceding RAPID trial [see Adverse Reactions (6.1)].

6.1 Clinical Trials Experience

Because clinical trials are conducted under widely varying conditions, adverse reaction rates observed in the clinical trials of a drug product cannot be directly compared to rates in the clinical trials of another drug and may not reflect the rates observed in clinical practice.

The following clinical trials were conducted with ZEMAIRA:

- Controlled, double-blind trial in 44 subjects, who received a weekly 60 mg/kg body weight dose of either ZEMAIRA (30 subjects) or Prolastin® (a commercially available Alpha1-Proteinase Inhibitor [Human] product) (14 subjects) for 10 weeks, followed by an open-label phase in which 43 subjects received ZEMAIRA weekly for 14 weeks;
- Open-label trial in 9 subjects who received a weekly 60 mg/kg body weight dose of ZEMAIRA for 26 weeks, followed by a 7-week to 22-week extension;
- Crossover, double-blind trial in 18 subjects who received a single 60 mg/kg dose of ZEMAIRA and a single 60 mg/kg dose of Prolastin;
- Open-label trial of 19 subjects who received a single 15 mg/kg (2 subjects), 30 mg/kg (5 subjects), 60 mg/kg (6 subjects), or 120 mg/kg (6 subjects) dose of ZEMAIRA; and
- Post-Licensure Randomized, Placebo-Controlled Trial of Augmentation Therapy in Alpha-1 Protease Inhibitor Deficiency (RAPID), in 180 subjects who received a weekly 60 mg/kg body weight dose of either ZEMAIRA (93 subjects) or placebo (87 subjects) for 24 months (referred to as years 1 and 2 in Table 3).
- Post-Licensure Open-label extension of the RAPID trial involving 140 subjects who had completed blinded treatment with ZEMAIRA or placebo for 24 months in the RAPID trial and who entered the extension trial and received open-label ZEMAIRA for up to an additional 24 months (referred to as years 3 and 4 in Table 3).

Table 1 summarizes the ARs, expressed as events per subject-year, and the corresponding number of ARs per infusion, expressed as % of all infusions, for each treatment in pre-licensure clinical trials of ZEMAIRA.

Table 1. Overall Adverse Reactions (ARs) and Serious ARs
 | Number of Subjects [Based on unique subjects. If a subject experienced more than one AR, the subject was only counted once.] (Events per Subject-Year [The exposure adjusted event rate was based on total exposure time presented in subject-years and the total number of adverse reactions in the database.]) |  | Number of Infusions [If there were multiple occurrences of ARs following a single infusion, only one occurrence was counted.] (% of all Infusions)
 | ZEMAIRA (n=66, SY [SY=subject-year.] =28.72) | Prolastin (n=32), SY=3.83) | ZEMAIRA (n=1296) | Prolastin (n=160)
ARs (AEs assessed by investigator as at least possibly related or occurring during or within 72 hours after the end of the infusion or for which causality assessment was missing or indeterminate). | 54 (5.6) | 16 (3.8) | 160 (12.3) | 31 (19.4)
Serious ARs (Serious AEs assessed by investigator as at least possibly related or occurring during or within 72 hours after the end of the infusion or for which causality assessment was missing or indeterminate). | 4 (0.2) | 1 (1.0) | 6 (0.5) | 1 (0.6)

Table 2 summarizes the ARs occurring in 5% or more (>3) subjects, expressed as events per subject-year, and the corresponding number of ARs per infusion, expressed as % of all infusions, for each treatment in clinical trials of ZEMAIRA.

Table 2. Adverse Reactions Occurring in ≥5% of Subjects
ARs (AEs assessed by investigator as at least possibly related or occurring during or within 72 hours after the end of the infusion or for which causality assessment was missing or indeterminate). | Number of Subjects [Based on unique subjects. If a subject experienced more than one AR of the same type, the subject was only counted once.] (Events per Subject-Year [The exposure adjusted event rate was based on total exposure time presented in subject-years and the total number of adverse reactions in the database.]) |  | Number of Infusions [If more than one of the same type of an event occurred after an infusion, only one event was counted.] (% of all Infusions)
ARs (AEs assessed by investigator as at least possibly related or occurring during or within 72 hours after the end of the infusion or for which causality assessment was missing or indeterminate). | ZEMAIRA (n=66, SY [SY=subject-year.] =28.72) | Prolastin (n=32, SY=3.83) | ZEMAIRA (n=1296) | Prolastin (n=160)
Headache | 13 (0.7) | 5 (1.3) | 19 (1.5) | 5 (3.1)
Sinusitis | 10 (0.5) | 1 (0.3) | 13 (1.0) | 1 (0.6)
Upper Respiratory Infection | 10 (0.4) | 1 (0.3) | 10 (0.8) | 1 (0.6)
Bronchitis | 5 (0.2) | 0 (0.0) | 6 (0.5) | 0 (0.0)
Asthenia | 5 (0.2) | 2 (0.5) | 5 (0.4) | 2 (1.3)
Cough Increased | 5 (0.2) | 1 (0.5) | 5 (0.4) | 2 (1.3)
Fever | 4 (0.1) | 0 (0.0) | 4 (0.3) | 0 (0.0)
Injection Site Hemorrhage | 4 (0.1) | 0 (0.0) | 4 (0.3) | 0 (0.0)
Rhinitis | 4 (0.1) | 0 (0.0) | 4 (0.3) | 0 (0.0)
Sore Throat | 4 (0.1) | 0 (0.0) | 4 (0.3) | 0 (0.0)
Vasodilation | 4 (0.1) | 1 (0.3) | 4 (0.3) | 1 (0.6)

Diffuse interstitial lung disease was noted on a routine chest x-ray of one subject at Week 24. Causality could not be determined.

Chronic Obstructive Pulmonary Disease (COPD) Exacerbations

In a retrospective analysis, during the 10-week blinded portion of the 24-week clinical trial, 6 subjects (20%) of the 30 treated with ZEMAIRA had a total of 7 exacerbations of their chronic obstructive pulmonary disease (COPD). Nine subjects (64%) of the 14 treated with Prolastin had a total of 11 exacerbations of their COPD. The observed difference between groups was 44% (95% confidence interval [CI] from 8% to 70%). Over the entire 24-week treatment period, of the 30 subjects in the ZEMAIRA treatment group, 7 subjects (23%) had a total of 11 exacerbations of their COPD.

In the RAPID study 25 serious exacerbations of COPD were reported in 15 ZEMAIRA subjects vs. 17 such events in 9 placebo subjects, corresponding to rates of 0.146 exacerbations per subject-year with ZEMAIRA and 0.115 exacerbations per subject-year with placebo, (ratio ZEMAIRA:Placebo [95% confidence interval]: 1.256 [0.457 - 3.454]).

Subjects who were randomized to ZEMAIRA in the 2-year RAPID trial who then entered and received open-label ZEMAIRA in the 2 year RAPID extension trial were in the "Early Start" group. Subjects who were randomized to Placebo in the 2-year RAPID trial who then entered and received open-label ZEMAIRA in the 2 year RAPID extension trial were in the "Delayed Start" group. During the RAPID Extension trial 37 serious exacerbations of COPD were reported in 19 subjects (25%) in the Early Start group, corresponding to rates of 0.25 exacerbations per subject-year. In comparison, 20 serious exacerbations were reported in 11 subjects (17%) in the Delayed Start group corresponding to rates of 0.16 exacerbations per subject-year (ratio Early: Delayed [95% confidence interval]: 1.58 [0.68 – 3.66], Table 3). Among the Early Start subjects who entered the RAPID extension trial (N = 76), the exposure adjusted incidence rate of serious exacerbations during the RAPID extension trial (years 3-4) was 0.25 compared to 0.12 for those subjects during the earlier RAPID trial (years 1-2), (ratio RAPID Extension:RAPID: 2.10 [95% confidence interval: 1.21 – 3.67]). Among the Delayed Start subjects who entered the RAPID extension trial (N = 64), the exposure adjusted incidence rate of serious exacerbations during the RAPID extension trial (years 3-4) was 0.16 compared to 0.10 for those subjects during the earlier RAPID trial (years 1-2), (ratio RAPID Extension:RAPID: 1.56 [95% confidence interval: 0.80 – 3.03]).

Table 3. Comparison of Exposure-Adjusted Incidence Rates (EAIR) for Serious COPD Exacerbations Occurring in the RAPID study between ZEMAIRA and Placebo subjects and in the RAPID Extension Studies between Early Start and Delayed Start subjects
Serious COPD Exacerbations [Episode = Serious exacerbations of COPD identified by investigators as meeting the Anthonisen criteria^1 plus Serious Adverse Event (SAE) terms COPD, Condition Aggravated, Bronchitis, Lower Respiratory Tract Infection, Pneumonia. Serious exacerbation events that overlap or occur within 1 day of one another were counted as single exacerbation episodes.] | Episode | n | % | EAIR (95% CI) | Episode | n | % | EAIR 95% CI | Treatment Ratio for EAIR (95% CI)
RAPID Study (Years 1 – 2) | ZEMAIRA (N = 93) |  |  |  | Placebo (N = 87) |  |  |  | ZEMAIRA: Placebo
RAPID Study (Years 1 – 2) | 25 | 15 | 16.1 | 0.15 (0.10-0.22) | 17 | 9 | 10.3 | 0.12 (0.07-0.18) | 1.26 (0.46 - 3.45)
Extension Study (Years 3-4) | Early Start [Early Start Group subjects were randomized to ZEMAIRA during the double-blind RAPID trial (years 1-2) and received open-label ZEMAIRA during the RAPID extension trial (years 3-4).] (N = 76) |  |  |  | Delayed Start [Delayed Start Group subjects were randomized to Placebo during the double-blind RAPID trial (years 1-2) and received open-label ZEMAIRA during the RAPID extension trial (years 3-4).] (N = 64) |  |  |  | Early: Delayed
Extension Study (Years 3-4) | 37 | 19 | 25.0 | 0.25 (0.18 – 0.35) | 20 | 11 | 17.2 | 0.16 (0.10 – 0.25) | 1.58 (0.68 – 3.66)
N = total number of safety subjects, n = number of subjects within a category, % = (n/N)*100, CI = Confidence Interval.
Subject time at risk: ZEMAIRA = 171.14 years, Placebo = 147.75 years, Early Start Group = 146.46 years, Delay Start Group = 124.71 years.
EAIR = Exposure-Adjusted Incidence Rate (events/subject time at risk). The point estimates and confidence intervals for EAIR values were calculated using negative binomial models.

In the 24-week double-blind trial, ZEMAIRA-treated subjects were tested for HAV, HBV, HCV, HIV, and parvovirus B19 (B19V), and no evidence of virus transmission was observed.

6.2 Immunogenicity

As with all therapeutic proteins, there is potential for immunogenicity. No anti-A1PI antibodies have been detected in clinical trials of ZEMAIRA. The detection of antibody formation is highly dependent on the sensitivity and specificity of the assay. Additionally, the observed incidence of antibody (including neutralizing antibody) positivity in an assay may be influenced by several factors including assay methodology, sample handling, timing of sample collection, concomitant medications, and underlying disease. For these reasons, comparison of the incidence of antibodies to ZEMAIRA with the incidence of antibodies to other products may be misleading.

6.3 Postmarketing Experience

Because postmarketing reporting of adverse reactions is voluntary and from a population of uncertain size, it is not always possible to reliably estimate the frequency of these reactions or establish a causal relationship to product exposure.

Table 4 lists the ARs that have been identified during postmarketing use of ZEMAIRA. This list does not include reactions already reported in clinical trials with ZEMAIRA [see Adverse Reactions (6.1)].

Table 4. ARs Reported During the Postmarketing Use of ZEMAIRA
System Organ Class | Preferred Term/Symptoms
Blood and lymphatic system disorders | Lymph node pain
Gastrointestinal disorders | Nausea
General disorders and administration site conditions | Chills, infusion site reactions, facial, periorbital, lip and extremity swelling, chest pain
Nervous system disorders | Hypoesthesia, paresthesia, dizziness
Skin disorders | Hyperhidrosis, pruritus, rash including exfoliative and generalized, urticaria
Vascular disorders | Flushing

8 USE IN SPECIFIC POPULATIONS

8.1 Pregnancy

Risk Summary

No animal reproduction studies have been conducted with Zemaira and its safety for use in human pregnancy has not been established in controlled clinical trials. Since alpha1-proteinase inhibitor is an endogenous human protein, it is considered unlikely that Zemaira will cause harm to the fetus when given at recommended doses. However, Zemaira should be given with caution to pregnant women. In the U.S. general population, the estimated background risk of major birth defect and miscarriage in clinically recognized pregnancies is 2-4% and 15-20%, respectively.

8.2 Lactation

Risk Summary

There is no information regarding the excretion of ZEMAIRA in human milk, the effect on the breastfed infant, or the effects on milk production. The developmental and health benefits of breastfeeding should be considered along with the mother's clinical need for ZEMAIRA and any potential adverse effects on the breastfed infant from ZEMAIRA or from the underlying maternal condition.

8.4 Pediatric Use

Safety and effectiveness in the pediatric population have not been established.

8.5 Geriatric Use

The safety and efficacy of ZEMAIRA in the geriatric population have not been established due to an insufficient number of subjects.

11 DESCRIPTION

ZEMAIRA is a sterile, white to off-white, lyophilized preparation of purified alpha1-proteinase inhibitor (human) (A1-PI), also known as alpha1-antitrypsin, to be reconstituted and administered by the intravenous route. The specific activity of ZEMAIRA is ≥0.7 mg of functional A1-PI per milligram of total protein. The purity (total A1-PI/total protein) is ≥90% A1-PI. Each vial contains approximately 1000 mg, 4000 mg or 5000 mg of functionally active A1-PI. The measured amount per vial of functionally active A1-PI as determined by its capacity to neutralize human neutrophil elastase (NE) is printed on the vial label and carton. Following reconstitution with 20 mL, 76 mL or 95 mL of Sterile Water for Injection, USP, the ZEMAIRA solution contains 73 to 89 mM sodium, 30 to 39 mM chloride, 15 to 20 mM phosphate, and 121 to 168 mM mannitol. Hydrochloric acid and/or sodium hydroxide may have been added to adjust the pH. ZEMAIRA contains no preservative.

All plasma used in the manufacture of ZEMAIRA is obtained from US donors and is tested using serological assays for HBsAg and antibodies to HIV-1/2 and HCV. The plasma is tested with Nucleic Acid Testing (NAT) for HBV, HCV, HIV-1, and HAV, and found to be nonreactive (negative). The plasma is also tested by NAT for B19V. Only plasma that passed the virus screening is used for production. The limit for B19V in the fractionation pool is ≤10^4 International Units of B19V per mL.

ZEMAIRA is manufactured from large pools of human plasma by cold ethanol fractionation according to a modified Cohn process followed by additional purification steps. The manufacturing process includes two virus clearance steps: heat treatment at 60°C for 10 hours in an aqueous solution with stabilizers; and nanofiltration. These virus clearance steps have been validated in a series of in vitro experiments for their capacity to inactivate/remove both enveloped and non-enveloped viruses. Table 5 shows the virus clearance capacity of the ZEMAIRA manufacturing process, expressed as mean log10 reduction factor.

Table 5. Cumulative (Log10) Virus Inactivation/Removal in ZEMAIRA
Manufacturing Step | Virus Reduction Factor (Log10)
Manufacturing Step | Enveloped Viruses |  |  |  | Non-Enveloped Viruses
Manufacturing Step | HIV-1 | BVDV | WNV | PRV | HAV | CPV
Heat treatment [Studies using B19V, which are considered experimental in nature, have demonstrated a virus reduction factor of 1.9 log10.] [At 60°C for 10 hours.] | ≥6.8 | ≥5.2 | ≥8.3 | 4.4 | ≥5.4 | na
Nanofiltration | ≥5.5 | ≥5.4 | ≥8.4 | ≥6.3 | ≥5.3 | ≥6.4
Cumulative Virus Reduction (log10) | ≥12.3 | ≥10.6 | ≥16.7 | ≥10.7 | ≥10.7 | ≥6.4
HIV, human immunodeficiency virus type 1, a model for HIV-1 and HIV-2.
BVDV, bovine viral diarrhea virus, a model for HCV.
WNV, West Nile virus.
PRV, pseudorabies virus, a non-specific model for large DNA viruses, e.g., herpes.
HAV, hepatitis A virus.
CPV, canine parvovirus, model for B19V.
na, not applicable.

12 CLINICAL PHARMACOLOGY

12.1 Mechanism of Action

A1-PI deficiency is a chronic, hereditary, autosomal, co-dominant disorder that is usually fatal in its severe form. Low blood levels of A1-PI (i.e., below 11 µM) are most commonly associated with progressive, severe emphysema that becomes clinically apparent by the third to fourth decade of life. In addition, PiSZ individuals, whose serum A1-PI levels range from approximately 9 to 23 µM, are considered to have a moderately increased risk for developing emphysema, regardless of whether their serum A1-PI levels are above or below 11 µM.^2 Not all individuals with severe genetic variants of A1-PI deficiency have emphysema. Augmentation therapy with alpha1-proteinase inhibitor (human) is indicated only in patients with severe congenital A1-PI deficiency who have clinically evident emphysema. A registry study showed 54% of A1-PI deficient subjects had emphysema.^3 Another registry study showed 72% of A1-PI deficient subjects had pulmonary symptoms.^4 Smoking is an important risk factor for the development of emphysema in patients with A1-PI deficiency.

Approximately 100 genetic variants of A1-PI deficiency can be identified electrophoretically, only some of which are associated with the clinical disease.^5,6 Ninety-five percent of clinically symptomatic A1-PI deficient individuals are of the severe PiZZ phenotype. Up to 39% of A1-PI deficient patients may have an asthmatic component to their lung disease, as evidenced by symptoms and/or bronchial hyperreactivity.^3 Pulmonary infections, including pneumonia and acute bronchitis, are common in A1-PI deficient patients and contribute significantly to the morbidity of the disease.

Augmenting the levels of functional protease inhibitor by intravenous infusion is an approach to therapy for patients with A1-PI deficiency. However, the efficacy of augmentation therapy in affecting the progression of emphysema has not been demonstrated in randomized, controlled clinical studies. The intended theoretical goal is to provide protection to the lower respiratory tract by correcting the imbalance between NE and protease inhibitors. Whether augmentation therapy with ZEMAIRA or any A1-PI product actually protects the lower respiratory tract from progressive emphysematous changes has not been evaluated. Individuals with endogenous levels of A1-PI below 11 µM, in general, manifest a significantly increased risk for development of emphysema above the general population background risk.^6,7,8,9 Although the maintenance of blood serum levels of A1-PI (antigenically measured) above 11 µM has been historically postulated to provide therapeutically relevant anti-neutrophil elastase protection^10, this has not been proven. Individuals with severe A1-PI deficiency have been shown to have increased neutrophil and NE concentrations in lung epithelial lining fluid compared to normal PiMM individuals, and some PiSZ individuals with A1-PI above 11 µM have emphysema attributed to A1-PI deficiency.^2 These observations underscore the uncertainty regarding the appropriate therapeutic target serum level of A1-PI during augmentation therapy.

Pulmonary disease, particularly emphysema, is the most frequent manifestation of A1-PI deficiency.^6 The pathogenesis of emphysema is understood to evolve as described in the "protease-antiprotease imbalance" model. A1-PI is now understood to be the primary antiprotease in the lower respiratory tract, where it inhibits NE.^11 Normal healthy individuals produce sufficient A1-PI to control the NE produced by activated neutrophils and are thus able to prevent inappropriate proteolysis of lung tissue by NE. Conditions that increase neutrophil accumulation and activation in the lung, such as respiratory infection and smoking, will in turn increase levels of NE. However, individuals who are severely deficient in endogenous A1-PI are unable to maintain an appropriate antiprotease defense and are thereby subject to more rapid proteolysis of the alveolar walls leading to chronic lung disease. ZEMAIRA serves as A1-PI augmentation therapy in this patient population, acting to increase and maintain serum levels and ELF levels of A1-PI.

12.2 Pharmacodynamics

Weekly repeated infusions of A1-PI at a dose of 60 mg/kg lead to serum A1-PI levels above the historical target threshold of 11 µM.

The clinical benefit of the increased blood levels of A1-PI at the recommended dose has not been established for any A1-PI product.

12.3 Pharmacokinetics

A double-blind, randomized, active-controlled, crossover pharmacokinetic study was conducted in 13 males and 5 females with A1-PI deficiency, ranging in age from 36 to 66 years. Nine subjects received a single 60 mg/kg dose of ZEMAIRA followed by Prolastin, and 9 subjects received Prolastin followed by a single 60 mg/kg dose of ZEMAIRA, with a wash-out period of 35 days between doses. A total of 13 post-infusion serum samples were taken at various time points up to Day 21. Table 6 shows the mean results for the ZEMAIRA pharmacokinetic parameters.

Table 6. Pharmacokinetic Parameters for Antigenic A1-PI in 18 Subjects Following a Single 60 mg/kg Dose of ZEMAIRA
Pharmacokinetic Parameter | Mean (SD) [n=18 subjects.]
Area under the curve (AUC0-∞) | 144 (±27) µM × day
Maximum concentration (Cmax) | 44.1 (±10.8) µM
Terminal half-life (t1/2ß) | 5.1 (±2.4) days
Total clearance | 603 (±129) mL/day
Volume of distribution at steady state | 3.8 (±1.3) L

13 NONCLINICAL TOXICOLOGY

13.1 Carcinogenesis, Mutagenesis, Impairment of Fertility

Long-term studies in animals to evaluate carcinogenesis, mutagenesis, or impairment of fertility have not been conducted.

13.2 Animal Toxicology and/or Pharmacology

In a safety pharmacology study, dogs were administered a 60 or 240 mg/kg intravenous dose of ZEMAIRA. At the clinical dose of 60 mg/kg, no changes in cardiovascular and respiratory parameters or measured hematology, blood chemistry, or electrolyte parameters were attributed to the administration of ZEMAIRA. A minor transient decrease in femoral resistance and increase in blood flow were observed after administration of the 240 mg/kg dose.

In single-dose studies, mice and rats were administered a 0, 60, 240, or 600 mg/kg intravenous dose of ZEMAIRA and observed twice daily for 15 days. No signs of toxicity were observed up to 240 mg/kg. Transient signs of distress were observed in male mice and in male and female rats after administration of the highest dose (600 mg/kg).

In repeat-dose toxicity studies, rats and rabbits received 0, 60, or 240 mg/kg intravenous doses of ZEMAIRA once daily for 5 consecutive days. No treatment-related effects on clinical signs, body weight, hematology, coagulation, or urinalysis were observed in rats administered up to 240 mg/kg. No signs of toxicity were observed in rabbits administered 60 mg/kg. Changes in organ weights and minimal epidermal ulceration were observed in rabbits administered 240 mg/kg, but had no clinical effects.

The local tolerance of ZEMAIRA was evaluated in rabbits following intravenous, perivenous, and intraarterial administration. No treatment-related local adverse reactions were observed.

14 CLINICAL STUDIES

Clinical trials were conducted pre-licensure with ZEMAIRA in 89 subjects (59 males and 30 females). The subjects ranged in age from 29 to 68 years (median age 49 years). Ninety-seven percent of the treated subjects had the PiZZ phenotype of A1-PI deficiency, and 3% had the MMALTON phenotype. At screening, serum A1-PI levels were between 3.2 and 10.1 µM (mean of 5.6 µM). The objectives of the clinical trials were to demonstrate that ZEMAIRA augments and maintains serum levels of A1-PI above 11 µM (80 mg/dL) and increases A1-PI levels in ELF of the lower lung.

In a double-blind, controlled clinical trial to evaluate the safety and efficacy of ZEMAIRA, 44 subjects were randomized to receive 60 mg/kg of either ZEMAIRA or Prolastin once weekly for 10 weeks. After 10 weeks, subjects in both groups received ZEMAIRA for an additional 14 weeks. Subjects were followed for a total of 24 weeks to complete the safety evaluation [see Adverse Reactions (6.1)]. The mean trough serum A1-PI levels at steady state (Weeks 7-11) in the ZEMAIRA-treated subjects were statistically equivalent to those in the Prolastin-treated subjects within a range of ±3 µM. Both groups were maintained above 11 µM. The mean (range and standard deviation [SD]) of the steady state trough serum antigenic A1-PI level for ZEMAIRA-treated subjects was 17.7 µM (range 13.9 to 23.2, SD 2.5) and for Prolastin-treated subjects was 19.1 µM (range 14.7 to 23.1, SD 2.2). The difference between the ZEMAIRA and the Prolastin groups was not considered clinically significant and may be related to the higher specific activity of ZEMAIRA.

In a subgroup of subjects enrolled in the trial (10 ZEMAIRA-treated subjects and 5 Prolastin-treated subjects), bronchoalveolar lavage was performed at baseline and at Week 11. Four A1-PI related analytes in ELF were measured: antigenic A1-PI, A1-PI:NE complexes, free NE, and functional A1-PI (ANEC). A blinded retrospective analysis, which revised the prospectively established acceptance criteria showed that within each treatment group, ELF levels of antigenic A1-PI and A1-PI:NE complexes increased from baseline to Week 11 (Table 7). Free elastase was immeasurably low in all samples. The post-treatment ANEC values in ELF were not significantly different between the ZEMAIRA-treated and Prolastin-treated subjects (mean 1725 nM vs. 1418 nM). No conclusions can be drawn about changes of ANEC values in ELF during the trial period as baseline values in the ZEMAIRA-treated subjects were unexpectedly high. No A1-PI analytes showed any clinically significant differences between the ZEMAIRA and Prolastin treatment groups.

Table 7. Change in ELF From Baseline to Week 11 in a Subgroup Analysis
Analyte | Treatment | Mean Change From Baseline | 90% CI
A1-PI (nM) | ZEMAIRA [n=10 subjects.] | 1358.3 | 822.6 to 1894.0
A1-PI (nM) | Prolastin [n=5 subjects.] | 949.9 | 460.0 to 1439.7
ANEC (nM) | ZEMAIRA | -588.1 | -2032.3 to 856.1
ANEC (nM) | Prolastin | 497.5 | -392.3 to 1387.2
A1-PI:NE Complexes (nM) | ZEMAIRA | 118.0 | 39.9 to 196.1
A1-PI:NE Complexes (nM) | Prolastin | 287.1 | 49.8 to 524.5
CI, confidence interval.

The clinical efficacy of ZEMAIRA or any A1-PI product in influencing the course of pulmonary emphysema or pulmonary exacerbations has not been demonstrated in adequately powered, randomized, controlled clinical trials.

15 REFERENCES

1. Anthonisen NR, Connett, JE, Kiley, JP, et al. Effects of Smoking Intervention and the Use of an Inhaled Anticholinergic Bronchodilator and on the Rate of Decline of FEV1 – The Lung Study. JAMA. 1994;272(19):1497-1505.
2. Turino GM, Barker AF, Brantly ML, et al. Clinical features of individuals with PI*SZ phenotype of α1-antitrypsin deficiency. Am J Respir Crit Care Med. 1996;154:1718-1725.
3. Stoller JK, Brantly M, et al. Formation and current results of a patient-organized registry for α1-antitrypsin deficiency. Chest. 2000;118(3):843-848.
4. McElvaney NG, Stoller JK, et al. Baseline characteristics of enrollees in the National Heart, Lung, and Blood Institute Registry of α1-Antitrypsin Deficiency. Chest. 1997;111:394-403.
5. Crystal RG. α1-antitrypsin deficiency, emphysema, and liver disease; genetic basis and strategies for therapy. J Clin Invest. 1990;85:1343-1352.
6. World Health Organization. Alpha-1-antitrypsin deficiency; Report of a WHO Meeting. Geneva. 18-20 March 1996.
7. Eriksson S. Pulmonary emphysema and alpha1-antitrypsin deficiency. ACTA Med Scand. 1964;175(2):197-205.
8. Eriksson S. Studies in α1-antitrypsin deficiency. ACTA Med Scan Suppl. 1965;432:1-85.
9. Gadek JE, Crystal RG. α1-antitrypsin deficiency. In: Stanbury JB, Wyngaarden JB, Frederickson DS, et al., eds. The Metabolic Basis of Inherited Disease. 5th ed. New York, NY: McGraw-Hill; 1983:1450-1467.
10. American Thoracic Society. Guidelines for the approach to the patient with severe hereditary alpha-1-antitrypsin deficiency. Am Rev Respir Dis. 1989;140:1494-1497.
11. Gadek JE, Fells GA, Zimmerman RL, Rennard SI, Crystal RG. Antielastases of the human alveolar structures; implications for the protease-antiprotease theory of emphysema. J Clin Invest. 1981;68:889-898.

16 HOW SUPPLIED/STORAGE AND HANDLING

ZEMAIRA is supplied in a single-dose vial containing the amount of functionally active A1-PI printed on the vial label and carton.

The product presentations include a package insert and the following components. Not made with natural rubber latex.

Table 8: How Supplied
Presentation | Kit NDC Number | Components
1000 mg of functionally active A1-PI | 0053-7201-02 | - ZEMAIRA in a single-dose vial [NDC 0053-7211-01] - 20 mL vial of Sterile Water for Injection, USP [NDC 0053-7653-20] - One Mix2Vial filter transfer set for reconstitution
4000 mg of functionally active A1-P1 | 0053-7202-02 | - ZEMAIRA in a single-dose vial [NDC 0053-7212-01] - 76 mL vial of Sterile Water for Injection, USP [NDC 0053-7653-80] - One Mix2Vial filter transfer set for reconstitution
5000 mg of functionally active A1-PI | 0053-7203-02 | - ZEMAIRA in a single-dose vial [NDC 0053-7213-01] - 95 mL vial of Sterile Water for Injection, USP [NDC 0053-7653-12] - One Mix2Vial filter transfer set for reconstitution

Storage and Handling

- When stored up to 25°C (77°F), ZEMAIRA is stable for the period indicated by the expiration date on its vial label and carton.
- Avoid freezing, which may damage the diluent vial.
- Discard any unused product and all used disposable supplies.

17 PATIENT COUNSELING INFORMATION

- Inform patients of the early signs of hypersensitivity reactions to ZEMAIRA (including hives, generalized urticaria, tightness of the chest, dyspnea, wheezing, faintness, hypotension, and anaphylaxis). Advise patients to discontinue use of ZEMAIRA and contact their physician and/or seek immediate emergency care, depending on the severity of the reaction, if these symptoms occur [see Warnings and Precautions (5.2)].
- Inform patients that because ZEMAIRA is made from human blood, it may carry a risk of transmitting infectious agents, e.g., viruses, the variant Creutzfeldt-Jakob disease (vCJD) agent and, theoretically, the Creutzfeldt-Jakob disease (CJD) agent [see Warnings and Precautions (5.3)].
- Inform patients that administration of ZEMAIRA has been demonstrated to raise the plasma level of A1-PI, but that the effect of this augmentation on the frequency of pulmonary exacerbations and on the rate of progression of emphysema has not been established by clinical trials.
- Dizziness may occur following the administration of ZEMAIRA; therefore, patients should rest for a while immediately following an infusion.

Manufactured by:
CSL Behring LLC
Kankakee, IL 60901 USA
US License No. 1767

For patent information: http://www.cslbehring.com/products/patents

Prolastin is a registered trademark of Grifols Therapeutics Inc.

Mix2Vial® is a registered trademark of West Pharma. Services IL, Ltd., a subsidiary of West Pharmaceuticals Services, Inc.

PRINCIPAL DISPLAY PANEL - Kit Carton

NDC 0053-7201-02
One single dose vial with diluent

1000 mg Range

Alpha1-Proteinase Inhibitor
(Human)
Zemaira®

For Intravenous Administration Only
Rx only

This package contains one vial of Zemaira®, one vial of Sterile Water for Injection, USP and
one Mix2Vial® filter transfer set for reconstitution.

Storage: Zemaira® stored up to 25°C (77°F) is stable for the period indicated by the expiration date
on the label. Avoid freezing, which may damage the diluent vial. Discard any unused product and
all used disposable supplies.

Manufactured by:
CSL Behring LLC
Kankakee, IL 60901 USA
US License No. 1767

CSL Behring

PRINCIPAL DISPLAY PANEL - 1000 mg Vial Label

1000 mg Range

NDC 0053-7211-01

Alpha1-Proteinase
Inhibitor (Human)

Zemaira®

Store up to 25ºC (77ºF).

Rx only
IV use only

Manufactured by:
CSL Behring LLC
Kankakee, IL 60901 USA
US License No. 1767

PRINCIPAL DISPLAY PANEL - 20 mL Vial Label

Sterile Water
for Injection,
USP, 20 mL

Manufactured by:
CSL Behring GmbH
35041 Marburg, Germany
US License No. 1765

Distributed by:
CSL Behring LLC
Kankakee, IL 60901 USA

PRINCIPAL DISPLAY PANEL - 4000 mg Range - Kit Carton

NDC 0053-7202-02
One single-dose vial with diluent

4000 mg Range

Alpha1-Proteinase Inhibitor
(Human)

Zemaira®

For Intravenous Administration Only
Rx only

This package contains one single-dose vial of Zemaira®, one vial of Sterile Water for Injection, USP and one
Mix2Vial® filter transfer set for reconstitution.

Storage: Zemaira® stored up to 25°C (77°F) is stable for the period indicated by the expiration date on the label.
Avoid freezing, which may damage the diluent vial.

Manufactured by:
CSL Behring LLC
Kankakee, IL 60901 USA
US License No. 1767

CSL Behring

PRINCIPAL DISPLAY PANEL - 4000 mg Vial Label

4000 mg Range

NDC 0053-7212-01

Alpha1-Proteinase
Inhibitor (Human)

Zemaira®

Store up to 25ºC (77ºF).

Rx only
IV use only

Manufactured by:
CSL Behring LLC
Kankakee, IL 60901 USA
US License No. 1767

PRINCIPAL DISPLAY PANEL - 76 mL Vial Label

Sterile Water
for Injection,
USP, 76 mL

Manufactured by:
CSL Behring LLC
Kankakee, IL 60901 USA

PRINCIPAL DISPLAY PANEL - 5000 mg Range - Kit Carton

NDC 0053-7203-02
One single dose vial with diluent

5000 mg Range

Alpha1-Proteinase Inhibitor
(Human)

Zemaira®

For Intravenous Administration Only
Rx only

This package contains one vial of Zemaira®, one vial of Sterile Water for Injection, USP and one
Mix2Vial® filter transfer set for reconstitution.

Storage: Zemaira® stored up to 25°C (77°F) is stable for the period indicated by the expiration date on the label.
Avoid freezing, which may damage the diluent vial.

Manufactured by:
CSL Behring LLC
Kankakee, IL 60901 USA
US License No. 1767

CSL Behring

PRINCIPAL DISPLAY PANEL - 5000 mg Vial Label

5000 mg Range

NDC 0053-7213-01

Alpha1-Proteinase
Inhibitor (Human)

Zemaira®

Store up to 25ºC (77ºF).

Rx only
IV use only

Manufactured by:
CSL Behring LLC
Kankakee, IL 60901 USA
US License No. 1767

PRINCIPAL DISPLAY PANEL - 95 mL Vial Label

Sterile Water
for Injection,
USP, 95 mL

Manufactured by:
CSL Behring LLC
Kankakee, IL 60901 USA